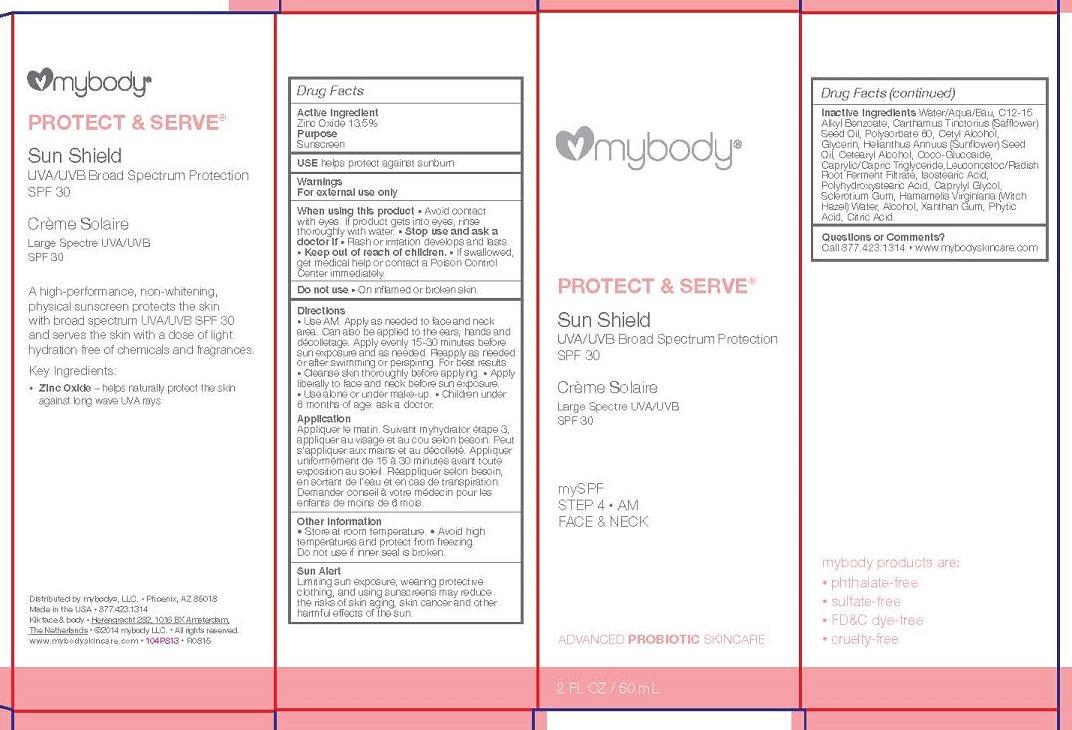 DRUG LABEL: myBody PROTECT AND SERVE
NDC: 49520-302 | Form: LOTION
Manufacturer: mybody
Category: otc | Type: HUMAN OTC DRUG LABEL
Date: 20150903

ACTIVE INGREDIENTS: TITANIUM DIOXIDE 11 g/100 mL; ZINC OXIDE 4 g/100 mL
INACTIVE INGREDIENTS: CYCLOMETHICONE 5; CYCLOMETHICONE; DIMETHICONE/VINYL DIMETHICONE CROSSPOLYMER (SOFT PARTICLE); METHYL METHACRYLATE/GLYCOL DIMETHACRYLATE CROSSPOLYMER; SORBITAN ISOSTEARATE; TRIBEHENIN; CALCIUM BEHENATE; MELANIN SYNTHETIC (TYROSINE, PEROXIDE); DIMETHICONOL (41 MPA.S); ALUMINUM OXIDE; PEG-10 DIMETHICONE (600 CST); METHICONE (20 CST); FERRIC OXIDE RED; CHOLECALCIFEROL; LYCOPENE; GLYCERIN; SUCROSE PALMITATE; LECITHIN, SOYBEAN

ACTIVE INGREDIENT

ZINCE OXIDE 13.5%

PURPOSE

SUNSCREEN

USE

HELPS PROTECT AGAINST SUNBURN

WARNINGS

FOR EXTERNAL USE ONLY

WHEN USING THIS PRODUCT

- AVOID CONTACT WITH EYES. IF PRODUCT GETS INTO EYES, RINSE THOROUGHLY WITH WATER.

STOP USE AND ASK A DOCTOR IF RASH OR IRRITATION DEVELOPS AND LASTS.

KEEP OUT OF REACH OF CHILDREN.

OTHER SAFETY INFORMATION

IF SWALLOWED, GET MEDICAL HELP OR CONTACT A POISON CONTROL CENTER IMMEDIATELY.

STORE AT ROOM TEMPERATURE.

AVOID HIGH TEMPERATURES AND PROTECT FROM FREEZING.

DO NOT USE IF INNER SEAL IS BROKEN.

DO NOT USE

- ON INFLAMED OR BROKEN SKIN.

Directions

- Use AM. Apply as needed to face and neck area. Can also be applied to the ears, hands and décolletage. Apply evenly 15-30 minutes before sun exposure and as needed. Reapply as needed or after swimming or perspiring. For best results
- Cleanse skin thoroughly before applying.
- Apply liberally to face and neck before sun exposure.
- Use alone or under make-up.
- Children under

6 months of age: ask a doctor.

GENERAL PRECAUTIONS

SUN ALERT

LIMITING SUN EXPOSURE, WEARING PROTECTIVE CLOTHING, AND USING SUNSCREENS MAY REDUCE THE RISKS OF SKIN AGING, SKIN CANCER AND OTHER HARMFUL EFFECTS OF THE SUN.

INACTIVE INGREDIENT

Inactive Ingredients Water/Aqua/Eau, C12-15 Alkyl Benzoate, Carthamus Tinctorius (Safflower) Seed Oil, Polysorbate 60, Cetyl Alcohol,
Glycerin, Helianthus Annuus (Sunflower) Seed Oil, Cetearyl Alcohol, Coco-Glucoside, Caprylic/Capric Triglyceride,Leuconostoc/Radish Root Ferment Filtrate, Isostearic Acid, Polyhydroxystearic Acid, Caprylyl Glycol, Sclerotium Gum, Hamamelis Virginiana (Witch Hazel) Water, Alcohol, Xanthan Gum, Phytic Acid, Citric Acid.

QUESTIONS OR COMMENTS?

CALL 877.423.1314 * WWW.MYBODYSKINCARE.COM